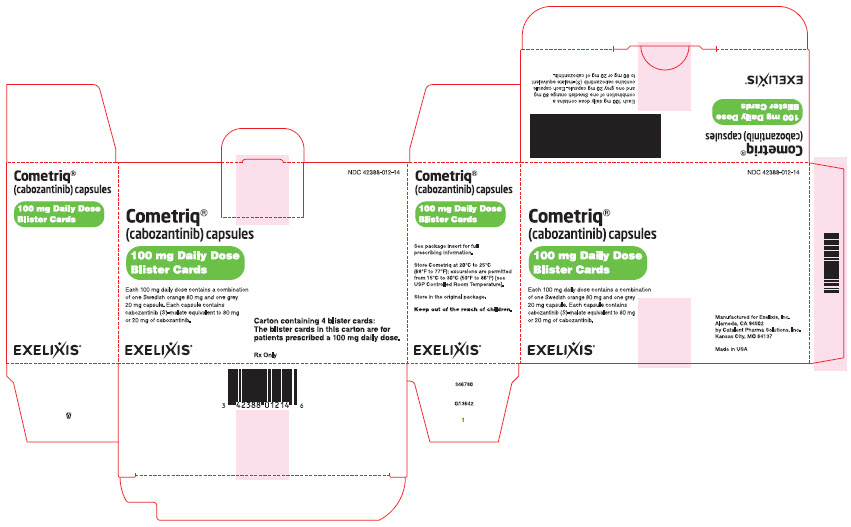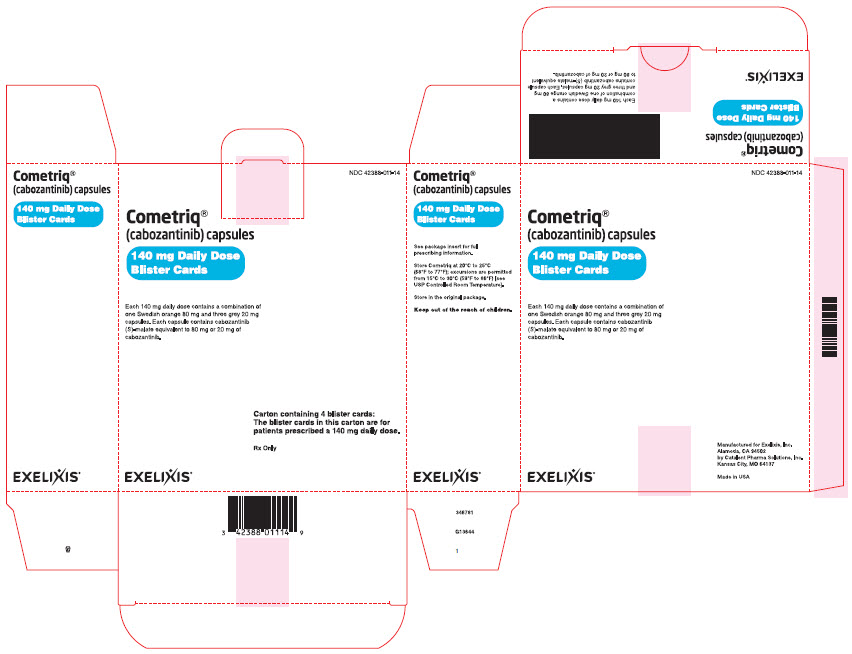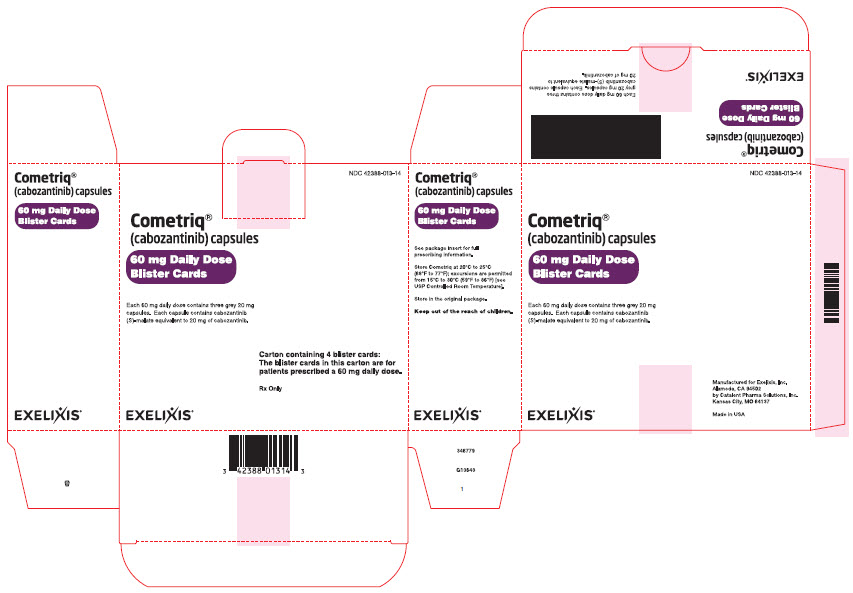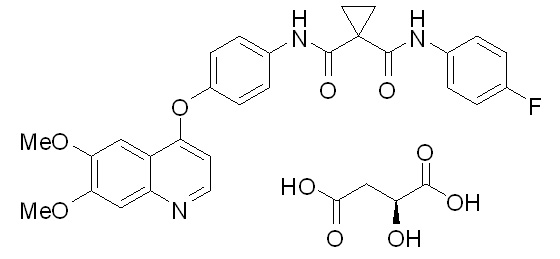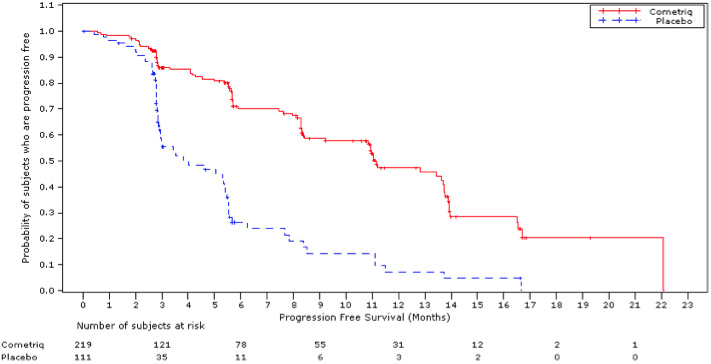 DRUG LABEL: COMETRIQ
NDC: 42388-011 | Form: KIT | Route: ORAL
Manufacturer: Exelixis, Inc.
Category: prescription | Type: HUMAN PRESCRIPTION DRUG LABEL
Date: 20251018

ACTIVE INGREDIENTS: cabozantinib s-malate 80 mg/1 1; cabozantinib s-malate 20 mg/1 1
INACTIVE INGREDIENTS: cellulose, microcrystalline; croscarmellose sodium; sodium starch glycolate type a potato; silicon dioxide; stearic acid; gelatin; ferric oxide red; ferrosoferric oxide; titanium dioxide; shellac; butyl alcohol; isopropyl alcohol; propylene glycol; ammonia; cellulose, microcrystalline; croscarmellose sodium; sodium starch glycolate type a potato; silicon dioxide; stearic acid; gelatin; ferrosoferric oxide; titanium dioxide; shellac; butyl alcohol; isopropyl alcohol; propylene glycol; ammonia

HIGHLIGHTS OF PRESCRIBING INFORMATION

These highlights do not include all the information needed to use COMETRIQ safely and effectively. See full prescribing information for COMETRIQ.
COMETRIQ® (cabozantinib) capsules, for oral use
Initial U.S. Approval: 2012

RECENT MAJOR CHANGES

Warnings and Precautions (5.6) 10/2025

1 INDICATIONS AND USAGE

COMETRIQ is a kinase inhibitor indicated for the treatment of patients with progressive, metastatic medullary thyroid cancer (MTC). (1)

2 DOSAGE AND ADMINISTRATION

- Recommended Dose: 140 mg orally, once daily. (2.1)
- Instruct patients not to eat for at least 2 hours before and at least 1 hour after taking COMETRIQ. (2.1)
- Do NOT substitute COMETRIQ capsules with cabozantinib tablets. (2.1)
- Hepatic Impairment: The recommended starting dose of COMETRIQ is 80 mg in patients with mild or moderate hepatic impairment. (2.1)

3 DOSAGE FORMS AND STRENGTHS

Capsules: 20 mg and 80 mg. (3)

4 CONTRAINDICATIONS

None. (4)

5 WARNINGS AND PRECAUTIONS

- Perforations and Fistulas: Monitor for symptoms. Discontinue COMETRIQ for Grade 4 fistula or perforation. (5.1)
- Hemorrhage: Do not administer COMETRIQ if recent history of hemorrhage. (5.2)
- Thrombotic Events: Discontinue COMETRIQ for myocardial infarction or serious arterial or venous thromboembolic events. (5.3)
- Impaired Wound Healing: Withhold COMETRIQ for at least 3 weeks before elective surgery. Do not administer for at least 2 weeks following major surgery and until adequate wound healing. The safety of resumption of COMETRIQ after resolution of wound healing complications has not been established. (5.4)
- Hypertension and hypertensive crisis: Monitor blood pressure regularly. Interrupt for hypertension that is not adequately controlled with anti- hypertensive therapy. Discontinue COMETRIQ for hypertensive crisis or severe hypertension that cannot be controlled with anti-hypertensive therapy. (5.5)
- Cardiac Failure: Monitor patients for signs and symptoms of cardiac failure throughout treatment. (5.6)
- Osteonecrosis of the Jaw (ONJ): Withhold COMETRIQ for at least 3 weeks prior to invasive dental procedure and for development of ONJ. (5.7)
- Diarrhea: May be severe. Interrupt COMETRIQ immediately until diarrhea resolves or decreases to Grade 1. Recommend standard antidiarrheal treatments. (5.8)
- Palmar-Plantar Erythrodysesthesia (PPE): Interrupt COMETRIQ until PPE resolves or decreases to Grade 1. (5.9)
- Proteinuria: Monitor urine protein. Discontinue for nephrotic syndrome. (5.10)
- Reversible Posterior Leukoencephalopathy Syndrome (RPLS): Discontinue COMETRIQ. (5.11)
- Embryo-Fetal Toxicity: Can cause fetal harm. Advise females of reproductive potential of the potential risk to a fetus and to use effective contraception. (5.12, 8.1, 8.3)
- Hypocalcemia: Monitor blood calcium levels and replace calcium as necessary during treatment. Withhold COMETRIQ and resume at reduced dose upon recovery or permanently discontinue COMETRIQ depending on severity. (5.13)

6 ADVERSE REACTIONS

- The most common adverse reactions (≥ 25%) are diarrhea, stomatitis, palmar-plantar erythrodysesthesia (PPE), decreased weight, decreased appetite, nausea, fatigue, oral pain, hair color changes, dysgeusia, hypertension, abdominal pain, and constipation.
- The most common laboratory abnormalities (≥ 25%) are increased AST, increased ALT, lymphopenia, increased alkaline phosphatase, hypocalcemia, neutropenia, thrombocytopenia, hypophosphatemia, and hyperbilirubinemia. (6.1)

To report SUSPECTED ADVERSE REACTIONS, contact Exelixis, Inc. at 1-855-500-3935 or FDA at 1-800-FDA-1088 or www.fda.gov/medwatch.

7 DRUG INTERACTIONS

- Strong CYP3A4 Inhibitors: Reduce the COMETRIQ dosage. (2.2, 7.1)
- Strong CYP3A4 Inducers: Increase the COMETRIQ dosage. (2.2, 7.2)

8 USE IN SPECIFIC POPULATIONS

- Lactation: Advise not to breastfeed. (8.2)

FULL PRESCRIBING INFORMATION

1 INDICATIONS AND USAGE

COMETRIQ is indicated for the treatment of patients with progressive, metastatic medullary thyroid cancer (MTC).

2 DOSAGE AND ADMINISTRATION

2.1 Recommended Dosage

Do NOT substitute COMETRIQ capsules with cabozantinib tablets.

The recommended daily dose of COMETRIQ is 140 mg once daily without food until disease progression or unacceptable toxicity. Instruct patients not to eat for at least 2 hours before and at least 1 hour after taking COMETRIQ.

Swallow COMETRIQ capsules whole. Do not open COMETRIQ capsules.

Do not take a missed dose within 12 hours of the next dose.

Do not ingest foods (e.g., grapefruit, grapefruit juice) or nutritional supplements that are known to inhibit cytochrome P450 while taking COMETRIQ.

2.2 Dosage Modifications for Adverse Reactions

Withhold COMETRIQ for NCI CTCAE Grade 4 hematologic adverse reactions, Grade 3 or greater non-hematologic adverse reactions, intolerable Grade 2 adverse reactions, or osteonecrosis of the jaw.

Upon resolution/improvement of the adverse reaction (i.e., return to baseline or resolution to Grade 1), reduce the dose as follows:

- If previously receiving 140 mg daily dose, resume treatment at 100 mg daily
- If previously receiving 100 mg daily dose, resume treatment at 60 mg daily
- If previously receiving 60 mg daily dose, resume at 60 mg if tolerated, otherwise, discontinue COMETRIQ

Permanently discontinue COMETRIQ for any of the following:

- development of gastrointestinal (GI) perforation or Grade 4 fistula
- severe hemorrhage
- acute myocardial infarction or arterial or venous thromboembolic events that require medical intervention
- nephrotic syndrome
- severe hypertension that cannot be controlled with anti-hypertensive therapy or Grade 4 hypertension
- reversible posterior leukoencephalopathy syndrome
- cardiac failure, depending on severity

2.3 Dosage Modifications for Coadministration with Strong CYP3A4 Inhibitors

Reduce the daily COMETRIQ dose by 40 mg (for example, from 140 mg to 100 mg daily or from 100 mg to 60 mg daily). Resume the dose that was used prior to initiating the CYP3A4 inhibitor 2 to 3 days after discontinuation of the strong inhibitor [see Drug Interactions (7.1), Clinical Pharmacology (12.3)].

2.4 Dosage Modifications for Coadministration with Strong CYP3A4 Inducers

Increase the daily COMETRIQ dose by 40 mg (for example, from 140 mg to 180 mg daily or from 100 mg to 140 mg daily) as tolerated. Resume the dose that was used prior to initiating the CYP3A4 inducer 2 to 3 days after discontinuation of the strong inducer. The daily dose of COMETRIQ should not exceed 180 mg [see Drug Interactions (7.2), Clinical Pharmacology (12.3)].

2.5 Dosage Modifications for Patients with Hepatic Impairment

The recommended starting dose of COMETRIQ for patients with mild to moderate hepatic impairment is 80 mg [see Use in Specific Populations (8.6), Clinical Pharmacology (12.3)].

3 DOSAGE FORMS AND STRENGTHS

Capsules:

20-mg gelatin capsules, grey with "XL184 20mg" printed in black on the body of the capsule.

80-mg gelatin capsules, Swedish orange with "XL184 80mg" printed in black on the body of the capsule.

4 CONTRAINDICATIONS

None

5 WARNINGS AND PRECAUTIONS

5.1 Perforations and Fistulas

Gastrointestinal (GI) perforations and fistulas, including fatal cases, were reported in 3% and 1% of COMETRIQ-treated patients (N=214), respectively. Non-GI fistulas including tracheal/esophageal, including fatal cases, were reported in 4% of COMETRIQ-treated patients.

Monitor patients for symptoms of perforations and fistulas, including abscess and sepsis. Discontinue COMETRIQ in patients who experience a Grade 4 fistula or a GI perforation [see Dosage and Administration (2.2)].

5.2 Hemorrhage

Severe and fatal hemorrhage occurred with COMETRIQ. The incidence of Grade ≥ 3 hemorrhagic events was higher in COMETRIQ-treated patients compared with placebo (3% vs. 1%).

Discontinue COMETRIQ for Grade 3 or 4 hemorrhage [see Dosage and Administration (2.2)]. Do not administer COMETRIQ to patients with a recent history of hemorrhage, including hemoptysis, hematemesis, or melena.

5.3 Thromboembolic Events

COMETRIQ increased the incidence of thrombotic events (venous thromboembolism: 6% vs. 3% and arterial thromboembolism: 2% vs. 0% in COMETRIQ-treated and placebo-treated patients, respectively).

Discontinue COMETRIQ in patients who develop an acute myocardial infarction or arterial or venous thromboembolic events that require medical intervention [see Dosage and Administration (2.2)].

5.4 Impaired Wound Healing

Wound complications have been reported with COMETRIQ. Withhold COMETRIQ for at least 3 weeks prior to elective surgery. Do not administer COMETRIQ for at least 2 weeks after major surgery and until adequate wound healing. The safety of resumption of COMETRIQ after resolution of wound healing complications has not been established.

5.5 Hypertension and Hypertensive Crisis

COMETRIQ can cause hypertension, including hypertensive crisis. Joint National Committee on Prevention, Detection, Evaluation, and Treatment of High Blood Pressure (modified JNC criteria) stage 1 or 2 hypertension was identified in 61% in COMETRIQ-treated patients compared with 30% of placebo-treated patients in the randomized trial [see Adverse Reactions (6.1)].

Do not initiate COMETRIQ in patients with uncontrolled hypertension. Monitor blood pressure regularly during COMETRIQ treatment. Withhold COMETRIQ for hypertension that is not adequately controlled with medical management; when controlled, resume COMETRIQ at a reduced dose. Discontinue COMETRIQ for severe hypertension that cannot be controlled with anti-hypertensive therapy and for hypertensive crisis [see Dosage and Administration (2.2)].

5.6 Cardiac Failure

COMETRIQ can cause severe and fatal cardiac failure [see Adverse Reactions (6.1)]. Cardiac failure occurred in 0.9% of patients treated with COMETRIQ as a single agent. Median time to onset of cardiac failure was 76 days (range: 60 days to 92 days).

Consider baseline and periodic evaluations of left ventricular ejection fraction. Monitor for signs and symptoms of cardiovascular events. Withhold and resume at a reduced dose upon recovery or permanently discontinue COMETRIQ depending on the severity [see Dosage and Administration (2.2)].

5.7 Osteonecrosis of the Jaw

Osteonecrosis of the jaw (ONJ) occurred in 1% of COMETRIQ-treated patients. ONJ can manifest as jaw pain, osteomyelitis, osteitis, bone erosion, tooth or periodontal infection, toothache, gingival ulceration or erosion, persistent jaw pain or slow healing of the mouth or jaw after dental surgery. Perform an oral examination prior to initiation of COMETRIQ and periodically during COMETRIQ therapy. Advise patients regarding good oral hygiene practices. Withhold COMETRIQ treatment for at least 3 weeks prior to scheduled dental surgery, or invasive dental procedures, if possible. Withhold COMETRIQ for development of ONJ until complete resolution [see Dosage and Administration (2.2)].

5.8 Diarrhea

Diarrhea occurred in 63% of patients treated with COMETRIQ. Grade 3-4 diarrhea occurred in 16% of patients treated with COMETRIQ [see Adverse Reactions (6.1)].

Withhold COMETRIQ until improvement to Grade 1 and resume COMETRIQ at a reduced dose for intolerable Grade 2 diarrhea, Grade 3 diarrhea that cannot be managed with standard antidiarrheal treatments, or Grade 4 diarrhea.

5.9 Palmar-Plantar Erythrodysesthesia

Palmar-plantar erythrodysesthesia (PPE) occurred in 50% of patients treated with COMETRIQ, including 13% Grade 3 [see Adverse Reactions (6.1)].

Withhold COMETRIQ until improvement to Grade 1 and resume COMETRIQ at a reduced dose for intolerable Grade 2 PPE or Grade 3 PPE.

5.10 Proteinuria

Proteinuria was observed in 2% of patients receiving COMETRIQ, including one with nephrotic syndrome. Monitor urine protein regularly during COMETRIQ treatment. Discontinue COMETRIQ in patients who develop nephrotic syndrome.

5.11 Reversible Posterior Leukoencephalopathy Syndrome

Reversible Posterior Leukoencephalopathy Syndrome (RPLS), a syndrome of subcortical vasogenic edema diagnosed by characteristic finding on MRI, occurred in one (<1%) patient. Perform an evaluation for RPLS in any patient presenting with seizures, headache, visual disturbances, confusion or altered mental function. Discontinue COMETRIQ in patients who develop RPLS [see Dosage and Administration (2.2)].

5.12 Embryo-Fetal Toxicity

Based on data from animal studies and its mechanism of action, COMETRIQ can cause fetal harm when administered to a pregnant woman. Cabozantinib administration to pregnant animals during organogenesis resulted in embryolethality at exposures below those occurring clinically at the recommended dose, and in increased incidences of skeletal variations in rats and visceral variations and malformations in rabbits. Advise pregnant women of the potential risk to a fetus. Advise females of reproductive potential to use effective contraception during treatment with COMETRIQ and for 4 months after the last dose [see Use in Specific Populations (8.1), (8.3), and Clinical Pharmacology (12.1)].

5.13 Hypocalcemia

COMETRIQ can cause hypocalcemia. Based on the safety population [see Clinical Trial Experience (6.1)], hypocalcemia occurred in 52% of patients treated with COMETRIQ, including Grade 3 or 4 in 12% of patients.

Monitor blood calcium levels and replace calcium as necessary during treatment. Withhold and resume at a reduced dose upon recovery or discontinue COMETRIQ depending on severity [see Dosage and Administration (2.2)].

6 ADVERSE REACTIONS

The following clinically significant adverse reactions are discussed elsewhere in the labeling:

- Perforations and Fistula [see Warnings and Precautions (5.1)]
- Hemorrhage [see Warnings and Precautions (5.2)]
- Thromboembolic Events [see Warnings and Precautions (5.3)]
- Impaired Wound Healing [see Warnings and Precautions (5.4)]
- Hypertension and Hypertensive Crisis [see Warnings and Precautions (5.5)]
- Cardiac Failure [see Warnings and Precautions (5.6)]
- Osteonecrosis of the Jaw [see Warnings and Precautions (5.7)]
- Diarrhea [see Warnings and Precautions (5.8)]
- Palmar-Plantar Erythrodysesthesia [see Warnings and Precautions (5.9)]
- Proteinuria [see Warnings and Precautions (5.10)]
- Reversible Posterior Leukoencephalopathy Syndrome [see Warnings and Precautions (5.11)]
- Hypocalcemia [see Warnings and Precautions (5.13)]

6.1 Clinical Trial Experience

Because clinical trials are conducted under widely varying conditions, adverse reaction rates observed in the clinical trials of a drug cannot be directly compared to rates in the clinical trials of another drug and may not reflect the rates observed in practice.

The safety of COMETRIQ was evaluated in 330 patients with progressive metastatic medullary thyroid cancer randomized to receive 140 mg COMETRIQ (n = 214) or placebo (n = 109) administered daily until disease progression or intolerable toxicity in a randomized, doubleblind, controlled trial (Study 1) [see Clinical Studies (14)]. The data described below reflect a median exposure to COMETRIQ for 204 days. The population exposed to COMETRIQ was 70% male, 90% white, and had a median age of 55 years.

Fatal adverse reactions occurred in 6% of patients receiving COMETRIQ and resulted from hemorrhage, pneumonia, septicemia, fistulas, cardiac arrest, respiratory failure, and unspecified death. Fatal adverse reactions occurred in 5% of patients receiving placebo and resulted from septicemia, pneumonia, and general deterioration.

The COMETRIQ dose was reduced in 79% of patients receiving COMETRIQ and in 9% of patients receiving placebo. The median number of dosing delays was one in patients receiving COMETRIQ and in no patients receiving placebo. Adverse reactions led to study treatment discontinuation in 16% of patients receiving COMETRIQ. The most frequent adverse reactions leading to permanent discontinuation of COMETRIQ were: hypocalcemia, increased lipase, PPE, diarrhea, fatigue, hypertension, nausea, pancreatitis, tracheal fistula formation and vomiting.

Increased levels of thyroid stimulating hormone (TSH) were observed in 57% of patients receiving COMETRIQ after the first dose compared to 19% of patients receiving placebo (regardless of baseline value). Ninety-two percent (92%) of patients on the COMETRIQ arm had a prior thyroidectomy, and 89% were taking thyroid hormone replacement prior to the first dose.

Adverse reactions which occurred in ≥ 25% of COMETRIQ-treated patients occurring more frequently in the COMETRIQ arm with a between-arm difference of ≥ 5% included, in order of decreasing frequency: diarrhea, stomatitis, palmar-plantar erythrodysesthesia (PPE), decreased weight, decreased appetite, nausea, fatigue, oral pain, hair color changes, dysgeusia, hypertension, abdominal pain, and constipation. The most common laboratory abnormalities (≥25%) were increased AST, increased ALT, lymphopenia, increased ALP, hypocalcemia, neutropenia, thrombocytopenia, hypophosphatemia, and hyperbilirubinemia. Grade 3-4 adverse reactions and laboratory abnormalities which occurred in ≥ 5% of COMETRIQ-treated patients occurring more frequently in the COMETRIQ arm with a between-arm difference of ≥ 2% included, in order of decreasing frequency; diarrhea, PPES, lymphopenia, hypocalcemia, fatigue, hypertension, asthenia, increased ALT, decreased weight, stomatitis, and decreased appetite (Table 1 and Table 2 summarize the adverse reactions and laboratory abnormalities reported in Study 1).

Table 1. Selected Adverse Reactions Occurring at a Higher Incidence in COMETRIQ-Treated Patients (Study 1) [Between Arm Difference of ≥ 5% (All Grades) [National Cancer Institute Common Terminology Criteria for Adverse Events Version 3.0] or ≥ 2% (Grades 3-4)]
System Organ Class/Preferred Terms | COMETRIQ (n=214) |  | Placebo (n=109)
System Organ Class/Preferred Terms | All Grades (%) | Grades 3-4 (%) | All Grades (%) | Grades 3-4 (%)
GASTROINTESTINAL DISORDERS
Diarrhea | 63 | 16 | 33 | 2
Stomatitis [Includes the following terms: stomatitis, aphthous stomatitis, mouth ulceration, mucosal inflammation] | 51 | 5 | 6 | 0
Nausea | 43 | 1 | 21 | 0
Oral pain [Includes the following terms: oral pain, oropharyngeal pain, glossitis, burning mouth syndrome, glossodynia] | 36 | 2 | 6 | 0
Constipation | 27 | 0 | 6 | 0
Abdominal pain [Includes the following terms: abdominal pain, abdominal pain lower, abdominal pain upper, abdominal rigidity, abdominal tenderness, esophageal pain] | 27 | 3 | 13 | 1
Vomiting | 24 | 2 | 2 | 1
Dysphagia | 13 | 4 | 6 | 1
Dyspepsia | 11 | 0 | 0 | 0
Hemorrhoids | 9 | 0 | 3 | 0
SKIN AND SUBCUTANEOUS TISSUE DISORDERS
PPE [Palmar-plantar erythrodysesthesia] | 50 | 13 | 2 | 0
Hair color changes/ depigmentation, graying | 34 | 0 | 1 | 0
Rash | 19 | 1 | 10 | 0
Dry skin | 19 | 0 | 3 | 0
Alopecia | 16 | 0 | 2 | 0
Erythema | 11 | 1 | 2 | 0
Hyperkeratosis | 7 | 0 | 0 | 0
INVESTIGATIONS
Decreased weight | 48 | 5 | 10 | 0
METABOLISM AND NUTRITION DISORDERS
Decreased appetite | 46 | 5 | 16 | 1
Dehydration | 7 | 2 | 2 | 1
GENERAL DISORDERS AND ADMINISTRATION SITE CONDITIONS
Fatigue | 41 | 9 | 28 | 3
Asthenia | 21 | 6 | 15 | 1
NERVOUS SYSTEM DISORDERS
Dysgeusia | 34 | 0 | 6 | 0
Headache | 18 | 0 | 8 | 0
Dizziness | 14 | 0 | 7 | 0
Paresthesia | 7 | 0 | 2 | 0
Peripheral sensory neuropathy | 7 | 0 | 0 | 0
Peripheral neuropathy | 5 | 0 | 0 | 0
VASCULAR DISORDERS
Hypertension | 33 | 8 | 4 | 0
Hypotension | 7 | 1 | 0 | 0
RESPIRATORY, THORACIC AND MEDIASTINAL DISORDERS
Dysphonia | 20 | 0 | 9 | 0
MUSCULOSKELETAL AND CONNECTIVE
TISSUE DISORDERS
Arthralgia | 14 | 1 | 7 | 0
Muscle spasms | 12 | 0 | 5 | 0
Musculoskeletal chest pain | 9 | 1 | 4 | 0
PSYCHIATRIC DISORDERS
Anxiety | 9 | 0 | 2 | 0

Table 2 Laboratory Abnormalities Occurring at a Higher Incidence in COMETRIQ-Treated Patients (Study 1) [Between Arm Difference of ≥ 5% (All Grades) or ≥ 2% (Grades 3-4)]
Test | COMETRIQ (n=214) |  | Placebo (N=109)
 | All Grades (%) | Grade 3-4 (%) | All Grades (%) | Grade 3-4 (%)
Chemistries
Increased AST | 86 | 3 | 35 | 2
Increased ALT | 86 | 6 | 41 | 2
Increased ALP | 52 | 3 | 35 | 3
Hypocalcemia | 52 | 12 | 27 | 3
Hypoalbuminemia | 43 | 2 | 16 | 0
Hypophosphatemia | 28 | 3 | 10 | 1
Hyperbilirubinemia | 25 | 2 | 14 | 5
Hypomagnesemia | 19 | 1 | 4 | 0
Hypokalemia | 18 | 4 | 9 | 3
Hyponatremia | 10 | 2 | 5 | 0
Hematologic
Lymphopenia | 53 | 16 | 51 | 11
Neutropenia | 35 | 3 | 15 | 2
Thrombocytopenia | 35 | 0 | 4 | 3
ALT, alanine aminotransferase; ALP, alkaline phosphatase; AST, aspartate aminotransferase

Nearly all COMETRIQ-treated patients (96% vs. 84% placebo) experienced elevated blood pressure and there was a doubling in the incidence of overt hypertension in COMETRIQ-treated patients over placebo-treated patients (61% vs. 30%) according to modified Joint National Committee on Prevention, Detection, Evaluation, and Treatment of High Blood Pressure (JNC) staging criteria. No patients developed malignant hypertension.

Table 3 Per-Patient Incidence of Hypertension (Study 1)
Hypertension, JNC [Joint National Committee on Prevention, Detection, Evaluation, and Treatment of High Blood Pressure, JAMA 2003: 289:2560. Criteria applied were modified, as multiple readings were not available per timepoint, and therefore not averaged.] Stage [Patients classified by highest category based on all recorded blood pressure readings beginning after the first dose through 30 days after last dose.] | COMETRIQ N=211 [Patients with at least two blood pressure measurements after the first dose] (%) | Placebo N=107(%)
Normal: Grade 0: Systolic < 120 mmHg and Diastolic < 80 mmHg | 4 | 15
Pre-hypertension: Systolic ≥ 120 mmHg or Diastolic ≥ 80 mmHg | 34 | 54
Stage 1: Systolic ≥ 140 mmHg or Diastolic ≥ 90 mmHg | 46 | 25
Stage 2: Systolic ≥ 160 mmHg or Diastolic ≥ 100 mmHg | 15 | 5
Malignant: Diastolic ≥ 120 mmHg | 0 | 0

Other clinically important adverse reactions (all grades) that were reported in clinical trials include: hepatitis cholestatic (<1%).

6.2 Postmarketing Experience

The following adverse reactions have been identified during postapproval use of COMETRIQ. Because these reactions are reported voluntarily from a population of uncertain size, it is not always possible to reliably estimate their frequency or establish a causal relationship to drug exposure.

Hematology: A case of supratherapeutic international normalized ratio (INR) and epistaxis during concomitant use of warfarin

Musculoskeletal and Connective Tissue Disorders: Extremity pain

Vascular Disorders: Arterial (including aortic) aneurysms, dissections, and rupture

7 DRUG INTERACTIONS

7.1 Effect of CYP3A4 Inhibitors

Administration of a strong CYP3A4 inhibitor, ketoconazole to healthy subjects increased single-dose plasma cabozantinib exposure by 38%. Avoid taking a strong CYP3A4 inhibitor (e.g., ketoconazole, itraconazole, clarithromycin, atazanavir, indinavir, nefazodone, nelfinavir, ritonavir, saquinavir, telithromycin, voriconazole) while taking COMETRIQ or reduce the dosage of COMETRIQ if concomitant use with strong CYP3A4 inhibitors cannot be avoided [see Dosage and Administration (2.2), Clinical Pharmacology (12.3)].

Avoid ingestion of foods (e.g., grapefruit, grapefruit juice) or nutritional supplements that are known to inhibit cytochrome P450 while taking COMETRIQ.

7.2 Effect of CYP3A4 Inducers

Administration of a strong CYP3A4 inducer, rifampin to healthy subjects decreased single-dose plasma cabozantinib exposure by 77%. Avoid chronic co-administration of strong CYP3A4 inducers (e.g., phenytoin, carbamazepine, rifampin, rifabutin, rifapentine, phenobarbital, St. John’s Wort) with COMETRIQ or increase the dosage of COMETRIQ if concomitant use with strong CYP3A4 inducers cannot be avoided [see Dosage and Administration (2.2), Clinical Pharmacology (12.3)].

7.3 Effect of MRP2 Inhibitors

Concomitant administration of MRP2 inhibitors may increase the exposure to cabozantinib. Monitor patients for increased toxicity when MRP2 inhibitors (e.g., abacavir, adefovir, cidofovir, furosemide, lamivudine, nevirapine, ritonavir, probenecid, saquinavir, and tenofovir) are co-administered with COMETRIQ [see Clinical Pharmacology (12.3)].

8 USE IN SPECIFIC POPULATIONS

8.1 Pregnancy

Risk Summary

Based on findings from animal studies and its mechanism of action, COMETRIQ can cause fetal harm when administered to a pregnant woman [see Clinical Pharmacology (12.1)]. There are no available data in pregnant women to inform the drug-associated risk. In animal developmental and reproductive toxicology studies administration of cabozantinib to pregnant rats and rabbits during organogenesis resulted in embryofetal lethality and structural anomalies at exposures that were below those occurring clinically at the recommended dose (see Data). Advise pregnant women or women of childbearing potential of the potential hazard to a fetus.

The estimated background risk of major birth defects and miscarriage for the indicated population is unknown. In the U.S. general population, the estimated background risk of major birth defects and miscarriage in clinically recognized pregnancies is 2-4% and 15-20%, respectively.

Data

Animal Data

In an embryo-fetal development study in pregnant rats, daily oral administration of cabozantinib throughout organogenesis caused increased embryo-fetal lethality compared to controls at a dose of 0.03 mg/kg (less than 1% of the human exposure by AUC at the 140 mg dose). Findings included delayed ossifications and skeletal variations at a dose of 0.01 mg/kg/day (approximately 0.03% of the human exposure by AUC at the 140 mg dose).

In pregnant rabbits, daily oral administration of cabozantinib throughout organogenesis resulted in findings of visceral malformations and variations including reduced spleen size and missing lung lobe at 3 mg/kg (approximately 11% of the human exposure by AUC at the 140 mg dose).

In a pre- and postnatal study in rats, cabozantinib was administered orally from gestation day 10 through postnatal day 20. Cabozantinib did not produce adverse maternal toxicity or affect pregnancy, parturition or lactation of female rats, and did not affect the survival, growth or postnatal development of the offspring at doses up to 0.3 mg/kg/day (approximately 0.02 times the recommended clinical dose of 140 mg based on body surface area).

8.2 Lactation

Risk Summary

There is no information regarding the presence of cabozantinib or its metabolites in human milk, or their effects on the breastfed infant, or milk production. Because of the potential for serious adverse reactions in a breastfed infant from COMETRIQ, advise a lactating woman not to breastfeed during treatment with COMETRIQ and for 4 months after the final dose.

8.3 Females and Males of Reproductive Potential

Pregnancy Testing

Verify the pregnancy status of females of reproductive potential prior to initiating COMETRIQ [see Use in Specific Populations (8.1)].

Contraception

COMETRIQ can cause fetal harm when administered to a pregnant woman [see Use in Specific Populations (8.1)].

Females

Advise females of reproductive potential to use effective contraception during treatment with COMETRIQ and for 4 months after the final dose.

Infertility

Females and Males

Based on findings in animals, COMETRIQ may impair fertility in females and males of reproductive potential [see Nonclinical Toxicology (13.1)].

8.4 Pediatric Use

The safety and effectiveness of COMETRIQ in pediatric patients have not been studied.

Juvenile Animal Toxicity Data

Juvenile rats were administered cabozantinib daily at doses of 1 or 2 mg/kg/day from Postnatal Day 12 (comparable to less than 2 years in humans) through Postnatal Day 35 or 70. Mortalities occurred at doses equal and greater than 1 mg/kg/day (approximately 0.07 times the clinical dose of 140 mg/day based on body surface area). Hypoactivity was observed at both doses tested on Postnatal Day 22. Targets were generally similar to those seen in adult animals, occurred at both doses, and included the kidney (nephropathy, glomerulonephritis), reproductive organs, gastrointestinal tract (cystic dilatation and hyperplasia in Brunner’s gland and inflammation of duodenum; and epithelial hyperplasia of colon and cecum), bone marrow (hypocellularity and lymphoid depletion), and liver. Tooth abnormalities and whitening as well as effects on bones including reduced bone mineral content and density, physeal hypertrophy, and decreased cortical bone also occurred at all dose levels. Recovery was not assessed at the 2 mg/kg dose level (approximately 0.14 times the clinical dose of 140 mg based on body surface area) due to high levels of mortality. At the low dose level, effects on bone parameters were partially resolved but effects on the kidney and epididymis/testis persisted after treatment ceased.

8.5 Geriatric Use

Clinical studies of COMETRIQ did not include sufficient numbers of patients aged 65 years and over to determine whether they respond differently from younger patients.

8.6 Hepatic Impairment

Increased exposure to cabozantinib has been observed in patients with mild to moderate hepatic impairment. Reduce the starting dose of COMETRIQ in patients with mild (Child-Pugh score (C-P) A) or moderate (C-P B) hepatic impairment. COMETRIQ is not recommended for use in patients with severe hepatic impairment [see Dosage and Administration (2.5), Clinical Pharmacology (12.3)].

8.7 Renal Impairment

Dosage adjustment is not required in patients with mild or moderate renal impairment. There is no experience with COMETRIQ in patients with severe renal impairment [see Clinical Pharmacology (12.3)].

10 OVERDOSAGE

One case of overdosage was reported in a patient who inadvertently took twice the intended dose (200 mg daily) for nine days. The patient suffered Grade 3 memory impairment, Grade 3 mental status changes, Grade 3 cognitive disturbance, Grade 2 weight loss, and Grade 1 increase in BUN. The extent of recovery was not documented.

11 DESCRIPTION

COMETRIQ is the (S)-malate salt of cabozantinib, a kinase inhibitor. Cabozantinib (S)-malate is described chemically as N-(4-(6,7-dimethoxyquinolin-4-yloxy)phenyl)-N'-(4-fluorophenyl)cyclopropane- 1,1-dicarboxamide, (2S)-hydroxybutanedioate. The molecular formula is C28H24FN3O5•C4H6O5 and the molecular weight is 635.6 Daltons as malate salt. The chemical structure of cabozantinib (S)-malate salt is:

Cabozantinib (S)-malate salt is a white to off-white solid that is practically insoluble in aqueous media.

COMETRIQ (cabozantinib) capsules for oral use are supplied as printed hard gelatin capsules containing cabozantinib (S)-malate equivalent to 20 mg or 80 mg cabozantinib and the following inactive ingredients: silicified microcrystalline cellulose, croscarmellose sodium, sodium starch glycolate, fumed silica, and stearic acid.

The grey gelatin capsule shells contain black iron oxide and titanium dioxide and the Swedish orange gelatin capsule shells contain red iron oxide, and titanium dioxide. The printing ink contains shellac glaze, black iron oxide, N-butyl alcohol, isopropyl alcohol, propylene glycol, and ammonium hydroxide.

12 CLINICAL PHARMACOLOGY

12.1 Mechanism of Action

In vitro biochemical and/or cellular assays have shown that cabozantinib inhibits the tyrosine kinase activity of RET, MET, VEGFR-1, -2 and -3, KIT, TRKB, FLT-3, AXL, ROS1, TYRO3, MER, and TIE-2. These receptor tyrosine kinases are involved in both normal cellular function and pathologic processes such as oncogenesis, metastasis, tumor angiogenesis, drug resistance, and maintenance of the tumor microenvironment.

12.2 Pharmacodynamics

Cardiac Electrophysiology

The effect of orally administered COMETRIQ 140 mg on QTc interval was evaluated in a randomized, double-blinded, placebo-controlled study in patients with MTC. A mean increase in QTcF of 10 - 15 ms was observed at 4 weeks after initiating COMETRIQ. A concentration-QTc relationship could not be definitively established. Changes in cardiac wave form morphology or new rhythms were not observed. No COMETRIQ-treated patients had a QTcF > 500 ms [see Clinical Studies (14)].

12.3 Pharmacokinetics

A population pharmacokinetic analysis of cabozantinib was performed using data collected from 289 patients with solid tumors including MTC following oral administration of 140 mg daily doses. Repeat daily dosing of COMETRIQ at 140 mg for 19 days resulted in 4- to 5-fold mean cabozantinib accumulation (based on AUC) compared to a single dose administration; steady state was achieved by Day 15.

Absorption

Following oral administration of COMETRIQ, median time to peak cabozantinib plasma concentrations (Tmax) ranged from 2 to 5 hours post-dose.

A 19% increase in the Cmax of the tablet formulation (CABOMETYX™) compared to the capsule formulation (COMETRIQ) was observed following a single 140 mg dose. A less than 10% difference in the AUC was observed between cabozantinib tablet (CABOMETYX) and capsule (COMETRIQ) formulations [see Dosage and Administration (2.1)].

Cabozantinib Cmax and AUC values increased by 41% and 57%, respectively, following a high-fat meal relative to fasted conditions in healthy subjects administered a single 140 mg oral COMETRIQ dose.

Distribution

The oral volume of distribution (V/F) of cabozantinib is approximately 349 L. Cabozantinib is highly protein bound in human plasma (≥ 99.7%).

Elimination

The predicted effective half-life is approximately 55 hours and the clearance (CL/F) at steady-state is estimated to be 4.4 L/hr.

Metabolism

Cabozantinib is a substrate of CYP3A4 in vitro.

Excretion

Approximately 81% of the total administered radioactivity was recovered within a 48-day collection period following a single 140 mg dose of an investigational ^14C-cabozantinib formulation in healthy subjects. Approximately 54% was recovered in feces and 27% in urine. Unchanged cabozantinib accounted for 43% of the total radioactivity in feces and was not detectable in urine following a 72 hour collection.

Specific Populations

The following patient characteristics did not result in a clinically relevant difference in the pharmacokinetics of cabozantinib: age (20-86 years), sex, race (Whites and non-Whites), or mild to moderate renal impairment (eGFR greater than or equal to 30 mL/min/1.73 m^2 as estimated by MDRD (modification of diet in renal disease equation)). The pharmacokinetics of cabozantinib is unknown in patients with worse than moderate renal impairment (eGFR less than 29 mL/min/1.73m^2) as estimated by MDRD equation or renal impairment requiring dialysis.

Patients with Hepatic Impairment

Following a single oral 60 mg COMETRIQ, mean AUC0-inf for cabozantinib increased by 81% in subjects with mild (Child-Pugh A) hepatic impairment and 63% in subjects with moderate (Child-Pugh B) hepatic impairment compared to subjects with normal hepatic function [see Dosage and Administration (2.5), Use in Specific Populations (8.6)].

The pharmacokinetics of cabozantinib has not been studied in patients with severe (Child-Pugh C) hepatic impairment [see Use in Specific Populations (8.6)].

Drug Interaction Studies

CYP3A4 Inhibition on Cabozantinib

Administration of a strong CYP3A4 inhibitor, ketoconazole (400 mg daily for 27 days) to healthy subjects increased single-dose plasma cabozantinib exposure (AUC0-inf) by 38%.

CYP3A4 Induction on Cabozantinib

Administration of a strong CYP3A4 inducer, rifampin (600 mg daily for 31 days) to healthy subjects decreased single-dose plasma cabozantinib exposure (AUC0-inf) by 77%.

Cabozantinib on CYP2C8 substrates

No clinically-significant effect on single-dose rosiglitazone (a CYP2C8 substrate) plasma exposure (Cmax and AUC) was observed when co-administered with cabozantinib at steady-state plasma concentrations (≥ 100 mg/day daily for a minimum of 21 days) in patients with solid tumors.

Gastric pH modifying agents on Cabozantinib

No clinically-significant effect on plasma cabozantinib exposure (AUC) was observed following co-administration of the proton pump inhibitor (PPI) esomeprazole (40 mg daily for 6 days) with a single dose of 100 mg cabozantinib to healthy volunteers.

In vitro Studies

Metabolic Pathways:

Inhibition of CYP3A4 reduced the formation of the XL184 N-oxide metabolite by >80%. Inhibition of CYP2C9 had a minimal effect on cabozantinib metabolite formation (i.e., a <20% reduction). Inhibition of CYP1A2, CYP2A6, CYP2B6, CYP2C8, CYP2C19, CYP2D6 and CYP2E1 had no effect on cabozantinib metabolite formation.

Although cabozantinib is an inhibitor of CYP2C8 in vitro, a clinical study of this potential interaction concluded that concurrent use did not result in a clinically relevant effect on CYP2C8 substrate exposure. Given this finding, other less sensitive substrates of pathways affected by cabozantinib in vitro (i.e., CYP2C9, CYP2C19, and CYP3A4) were not evaluated in a clinical study because, although a clinically relevant exposure effect cannot be ruled out, it is unlikely. Cabozantinib does not inhibit CYP1A2 and CYP2D6 isozymes in vitro.

Cabozantinib is an inducer of CYP1A1 mRNA; however, the clinical relevance of this finding is unknown. Cabozantinib does not induce CYP1A2, CYP2B6, CYP2C8, CYP2C9, CYP2C19 or CYP3A4.

Drug Transporter Systems:

Cabozantinib is an inhibitor, but not a substrate, of P-gp transport activities and has the potential to increase plasma concentrations of co-administered substrates of P-gp. The clinical relevance of this finding is unknown.

Cabozantinib is a substrate of MRP2 in vitro and MRP2 inhibitors have the potential to increase plasma concentrations of cabozantinib. The clinical relevance of this finding is unknown.

13 NONCLINICAL TOXICOLOGY

13.1 Carcinogenesis, Mutagenesis, Impairment of Fertility

The carcinogenic potential of cabozantinib has been evaluated in two species: rasH2 transgenic mice and Sprague-Dawley rats. In the 2-year rat carcinogenicity study, once daily oral administration of cabozantinib resulted in a statistically significant increase in the incidence of malignant/complex malignant pheochromocytoma in combination with benign pheochromocytoma or in benign pheochromocytoma alone in male rats at a dose of 1 mg/kg (approximately 0.6 times the human exposure by AUC at the recommended 140 mg dose). Cabozantinib was not carcinogenic in a 26-week carcinogenicity study in rasH2 transgenic mice at a slightly higher exposure than the intended human therapeutic exposure.

Cabozantinib was not mutagenic in vitro in the bacterial reverse mutation (Ames) assay and was not clastogenic in both the in vitro cytogenetic assay using human lymphocytes or in the in vivo mouse micronucleus assay.

Based on nonclinical findings, male and female fertility may be impaired by treatment with COMETRIQ. In a fertility study in which cabozantinib was administered to male and female rats at doses of 1, 2.5, and 5 mg/kg/day, male fertility was significantly compromised at doses equal to or greater than 2.5 mg/kg/day (approximately equal to the human exposure by AUC at the recommended dose), with a decrease in sperm counts and reproductive organ weights. In females, fertility was significantly reduced at doses equal to or greater than 1 mg/kg/day (approximately 50% of the human exposure by AUC at the 140 mg recommended dose) with a significant decrease in the number of live embryos and a significant increase in pre- and post-implantation losses.

Observations of effects on reproductive tract tissues in general toxicology studies were supportive of effects noted in the dedicated fertility study and included hypospermia and absence of corpora lutea in male and female dogs in a 6-month repeat dose study at exposures equal to 6% and 3%, respectively, the human exposure by AUC at the recommended dose. In addition, female rats administered 5 mg/kg/day for 14 days (approximately equal to the human exposure by AUC at the 140 mg recommended dose) exhibited ovarian necrosis.

14 CLINICAL STUDIES

The safety and efficacy of COMETRIQ was assessed in an international, multi-center, randomized, double-blind, controlled trial (Study 1) of 330 patients with metastatic medullary thyroid carcinoma (MTC). Patients were required to have evidence of actively progressive disease within 14 months prior to study entry confirmed by an Independent Radiology Review Committee (IRRC) masked to treatment assignment (89%) or the treating physician (11%). Patients were randomized (2:1) to receive COMETRIQ 140 mg (n = 219) or placebo (n = 111) orally once daily, without food, until disease progression determined by the treating physician or until intolerable toxicity. Randomization was stratified by age (≤ 65 years vs. > 65 years) and prior use of a tyrosine kinase inhibitor (TKI) (yes vs. no). No cross-over was allowed at the time of progression. The main efficacy outcome measures of progression-free survival (PFS), objective response (OR), and response duration were based on IRRC-confirmed events using modified RECIST criteria.

Of 330 patients randomized, 67% were male, the median age was 55 years, 23% were 65 years or older, 89% were white, 54% had a baseline ECOG performance status of 0, and 92% had undergone a thyroidectomy. The RET mutation status determined by a research-use assay was positive in 51%, negative in 14%, and was unknown in 35%. Twenty-five percent (25%) had two or more prior systemic therapies and 21% had been previously treated with a TKI.

A statistically significant prolongation in PFS was demonstrated among COMETRIQ-treated patients compared to those receiving placebo [HR 0.28 (95% CI: 0.19, 0.40); p<0.0001], with median PFS times of 11.2 months and 4.0 months in the COMETRIQ and placebo arms, respectively.

Partial responses were observed only among patients in the COMETRIQ arm (27% vs. 0; p<0.0001). The median duration of objective responses was 14.7 months (95% CI: 11.1, 19.3) for patients treated with COMETRIQ. There was no statistically significant difference in overall survival (median OS: 26.6 months in the COMETRIQ arm vs. 21.1 months in the placebo arm [HR = 0.85 (95% CI: 0.64, 1.12), p = 0.2409]).

Figure 1: Progression-Free Survival

16 HOW SUPPLIED/STORAGE AND HANDLING

COMETRIQ 20 mg capsules are supplied as hard gelatin capsules with grey cap and grey body, printed with "XL184 20mg" in black ink and containing cabozantinib (S)-malate salt equivalent to 20 mg cabozantinib.

COMETRIQ 80 mg capsules are supplied as hard gelatin capsules with Swedish orange cap and Swedish orange body, printed with "XL184 80mg" in black ink and containing cabozantinib (S)- malate salt equivalent to 80 mg cabozantinib.

COMETRIQ capsules are supplied as follows:
Cartons

- 140 mg daily-dose carton NDC#42388-011-14
  Containing four 140 mg daily-dose blister cards
  (each blister card contains seven 80-mg and twenty-one 20-mg capsules)
- 100 mg daily-dose carton NDC#42388-012-14
  Containing four 100 mg daily-dose blister cards
  (each blister card contains seven 80-mg and seven 20-mg capsules)
- 60 mg daily-dose carton NDC#42388-013-14
  Containing four 60 mg daily-dose blister cards
  (each blister card contains twenty-one 20-mg capsules)

Store COMETRIQ at 20°C to 25°C (68°F to 77°F); excursions are permitted from 15°C to 30°C (59°F to 86°F) [see USP Controlled Room Temperature].

17 PATIENT COUNSELING INFORMATION

Advise patients to read the FDA-approved patient labeling (Patient Information).

- Perforations and fistulas: Advise patients that gastrointestinal disorders such as diarrhea, nausea, vomiting, and constipation may develop during COMETRIQ treatment and to seek immediate medical attention if they experience persistent or severe abdominal pain because cases of gastrointestinal perforation and fistula have been reported in patients taking COMETRIQ [see Warnings and Precautions (5.1)].
- Hemorrhage: Instruct patients to contact their healthcare provider to seek immediate medical attention for signs or symptoms of unusual severe bleeding or hemorrhage [see Warnings and Precautions (5.2)].
- Thromboembolic events: Venous and arterial thrombotic events have been reported. Advise patients to report signs or symptoms of an arterial thrombosis. Venous thromboembolic events including pulmonary embolus have been reported. Advise patients to contact their health care provider if new onset of dyspnea, chest pain, or localized limb edema occurs [see Warnings and Precautions (5.3)].
- Impaired wound healing: Advise patients that COMETRIQ may impair wound healing. Advise patients to inform their healthcare provider of any planned surgical procedure [see Warnings and Precautions (5.4)].
- Hypertension and hypertensive crisis: Inform patients of the signs and symptoms of hypertension. Advise patients to undergo routine blood pressure monitoring and to contact their health care provider if blood pressure is elevated or if they experience signs or symptoms of hypertension [see Warnings and Precautions (5.5)].
- Cardiac failure: Advise patients that COMETRIQ can cause cardiac failure. Advise patients to immediately contact their healthcare provider for signs and symptoms of cardiac failure [see Warnings and Precautions (5.6)].
- Osteonecrosis of the jaw: Advise patients regarding good oral hygiene practices. Advise patients to immediately contact their healthcare provider for signs or symptoms associated with osteonecrosis of the jaw [see Warnings and Precautions (5.7)].
- Diarrhea: Advise patients to notify their healthcare provider at the first signs of poorly formed or loose stool or an increased frequency of bowel movements [see Warnings and Precautions (5.8)].
- Palmar-plantar erythrodysesthesia: Advise patients to contact their healthcare provider for progressive or intolerable rash [see Warnings and Precautions (5.9)].
- Reversible posterior leukoencephalopathy syndrome: Advise patients to immediately contact their health care provider for new onset or worsening neurological function [see Warnings and Precautions (5.11)].
- Embryo-fetal toxicity:
  - Advise females of reproductive potential of the potential risk to a fetus. Advise females of reproductive potential to inform their healthcare provider of a known or suspected pregnancy [see Warnings and Precautions (5.12), Use in Specific Populations (8.1)].
  - Advise patients of reproductive potential to use effective contraception during treatment with COMETRIQ and for at least 4 months after the final dose [see Use in Specific Populations (8.3)].
- Lactation: Advise women not to breastfeed during treatment with COMETRIQ and for 4 months following the last dose [see Use in Specific Populations (8.2)].
- Drug interactions: Advise patients to inform their healthcare provider of all prescription or nonprescription medications, vitamins or herbal products. Inform patients to avoid grapefruit, grapefruit juice, and St. John’s wort [see Drug Interactions (7.1), (7.2)].
- Hypocalcemia: Advise patients that COMETRIQ can cause low calcium levels and that their serum calcium levels should be monitored regularly during treatment. Advise patients to immediately contact their healthcare provider for signs or symptoms of hypocalcemia [see Warnings and Precautions (5.13)].

Important administration information

- Instruct patients not to eat for at least 2 hours before and at least 1 hour after taking COMETRIQ. Instruct patients that COMETRIQ capsules should not be opened or crushed and to take COMETRIQ capsules with a full glass (at least 8 ounces) of water.

Manufactured for Exelixis, Inc. Alameda, CA 94502

PATIENT INFORMATION
COMETRIQ® (Ko-me-trik)
cabozantinib
capsules

What is COMETRIQ?

COMETRIQ is a prescription medicine used to treat people with medullary thyroid cancer that has spread to other parts of the body.

It is not known if COMETRIQ is safe and effective in children.

Before you take COMETRIQ, tell your healthcare provider about all of your medical conditions including if you:

- have a recent history of coughing up blood or bleeding or any unusual bleeding
- have an open or healing wound
- have high blood pressure
- have heart problems
- have a low calcium level in your blood (hypocalcemia)
- plan to have any surgery, a dental procedure, or have had a recent surgery. You should stop taking COMETRIQ at least 3 weeks before planned surgery. See "What are the possible side effects of COMETRIQ?"
- have liver problems
- are pregnant or plan to become pregnant. COMETRIQ can harm your unborn baby.
  - If you are able to become pregnant, your healthcare provider will check your pregnancy status before you start treatment with COMETRIQ.
  - Females who are able to become pregnant should use effective birth control (contraception) during treatment and for 4 months after the final dose of COMETRIQ.
  - Talk to your healthcare provider about birth control methods that may be right for you.
  - If you become pregnant or think you are pregnant, tell your healthcare provider right away.
- are breastfeeding or plan to breastfeed. It is not known if COMETRIQ passes into your breast milk. Do not breastfeed during treatment and for 4 months after the final dose of COMETRIQ.

Tell your healthcare provider about all the medicines you take, including prescription or over-the-counter medicines, vitamins, and herbal supplements. COMETRIQ and certain other medicines may affect each other causing side effects.

How should I take COMETRIQ?

- Take COMETRIQ exactly as your healthcare provider tells you to take it.
- Do not take COMETRIQ with food. Do not eat for at least 2 hours before and at least 1 hour after taking COMETRIQ.
- Swallow COMETRIQ capsules whole with a full glass (at least 8 ounces) of water.
- Do not crush or open COMETRIQ capsules.
- If you miss a dose and your next dose is in less than 12 hours, take your next dose at the normal time. Do not make up the missed dose.

What should I avoid while taking COMETRIQ?

Do not drink grapefruit juice, eat grapefruit or take supplements that contain grapefruit or St. John's wort during treatment with COMETRIQ.

What are the possible side effects of COMETRIQ?

COMETRIQ may cause serious side effects, including:

- a tear in your stomach or intestinal wall (perforation) or an abnormal connection between 2 parts of your body (fistula) that may lead to death. Tell your healthcare provider right away if you get tenderness or pain in your stomach-area (abdomen) that is severe or that does not go away.
- bleeding (hemorrhage). COMETRIQ can cause severe bleeding that may lead to death. Tell your healthcare provider right away if you get any signs of bleeding during treatment with COMETRIQ, including:
  - coughing up blood or blood clots
  - vomiting blood or if your vomit looks like coffee-grounds
  - red or black (looks like tar) stools
  - menstrual bleeding that is heavier than normal
  - any unusual or heavy bleeding
- blood clots, stroke, heart attack, and chest pain. Get emergency help right away if you get:
  - swelling or pain in your arms or legs
  - shortness of breath
  - feel lightheaded or faint
  - sweating more than usual
  - numbness or weakness of your face, arm or leg, especially on one side of your body
  - sudden confusion, trouble speaking or understanding
  - sudden trouble seeing in one or both eyes
  - sudden trouble walking
  - dizziness, loss of balance or coordination
  - a sudden severe headache
- wound healing problems. Wound healing problems have happened in some people who take COMETRIQ. Tell your healthcare provider if you plan to have any surgery before or during treatment with COMETRIQ.
  - You should stop taking COMETRIQ at least 3 weeks before planned surgery.
  - Your healthcare provider should tell you when you may start taking COMETRIQ again after surgery.
- high blood pressure (hypertension). Hypertension is common with COMETRIQ and can be severe. Your healthcare provider will check your blood pressure before starting COMETRIQ and regularly during treatment with COMETRIQ. If needed, your healthcare provider may prescribe medicine to treat your high blood pressure. Tell your healthcare provider if you develop severe headaches, nose bleeds, tiredness or confusion, vision changes, chest pain, trouble breathing, irregular heartbeat, or blood in your urine.
- heart problems. COMETRIQ can cause heart failure. Your healthcare provider may check your heart function before and during treatment with COMETRIQ. Tell your healthcare provider right away if you get any of the following signs and symptoms:
  - feeling like your heart is pounding, racing, or beating irregularly
  - shortness of breath
  - swelling of your ankles or feet
  - feeling lightheaded
  - tiredness
- severe jaw bone problems (osteonecrosis). Your healthcare provider should examine your mouth before you start and during treatment with COMETRIQ. Tell your dentist that you are taking COMETRIQ. It is important for you to practice good mouth care during treatment with COMETRIQ. Tell your healthcare provider right away if you develop any symptoms of jaw problems including: jaw pain, toothache, or sores on your gums.
- diarrhea. Diarrhea is common with COMETRIQ and can be severe. If needed, your healthcare provider may prescribe medicine to treat your diarrhea. Tell your healthcare provider right away, if you have frequent loose, watery bowel movements.
- a skin problem called hand-foot skin reaction. Hand-foot skin reactions are common with COMETRIQ and can be severe. Tell your healthcare provider right away if you have rashes, redness, pain, swelling, or blisters on the palms of your hands or soles of your feet.
- protein in your urine and possible kidney problems. Symptoms may include swelling in your hands, arms, legs, or feet.
- Reversible Posterior Leukoencephalopathy Syndrome (RPLS). A condition called reversible posterior leukoencephalopathy syndrome can happen during treatment with COMETRIQ. Tell your healthcare provider right away if you have headaches, seizures, confusion, changes in vision, or problems thinking.
- decreased calcium level in your blood (hypocalcemia). COMETRIQ can cause you to have a decreased amount of calcium in your blood. Your healthcare provider will do blood tests to check you for this problem and give you calcium if needed. Tell your healthcare provider right away if you get any of the following signs or symptoms:
  - muscle stiffness or muscle spasms
  - numbness or tingling in your fingers, toes, or around your mouth
  - seizures
  - sudden weight gain
  - swelling of your arms, hands, legs, and ankles

Your healthcare provider may change your dose, temporarily stop, or permanently stop treatment with COMETRIQ if you have certain side effects.

The most common side effects of COMETRIQ include:

- diarrhea
- redness, swelling or pain in your mouth or throat, or mouth sores. Tell your healthcare provider if these symptoms prevent you from eating or drinking.
- weight loss
- decreased appetite
- nausea
- tiredness
- hair color turning lighter
- change in taste
- pain in your abdomen
- constipation

The most common abnormal blood test results with COMETRIQ include:

- increased liver function blood tests
- decreased white blood cell counts
- increased levels of enzyme called alkaline phosphatase in the blood (test for liver or bone problems)
- decreased calcium and phosphate blood le
- decreased platelet counts
- increased bilirubin blood levels

COMETRIQ may cause fertility problems in females and males, which may affect your ability to have children. Talk to your healthcare provider if you have concerns about fertility.

These are not all the possible side effects of COMETRIQ

Call your doctor for medical advice about side effects. You may report side effects to FDA at 1-800-FDA-1088.

How should I store COMETRIQ?

- Store COMETRIQ at room temperature between 68°F to 77°F (20°C to 25°C).

Keep COMETRIQ and all medicines out of the reach of children.

General information about the safe and effective use of COMETRIQ.

Medicines are sometimes prescribed for purposes other than those listed in a Patient Information leaflet. Do not use COMETRIQ for a condition for which it was not prescribed. Do not give COMETRIQ to other people, even if they have the same symptoms you have. It may harm them. You can ask your pharmacist or healthcare provider for information about COMETRIQ that is written for health professionals.

What are the ingredients in COMETRIQ?

Active ingredient: cabozantinib

Inactive ingredients: silicified microcrystalline cellulose, croscarmellose sodium, sodium starch glycolate, fumed silica, and stearic acid

Capsule shells: Grey gelatin capsule shells contain black iron oxide and titanium dioxide. Swedish orange gelatin capsule shells contain red iron oxide, and titanium dioxide.

The printing ink contains shellac glaze, black iron oxide, N-butyl alcohol, isopropyl alcohol, propylene glycol, and ammonium hydroxide.

Manufactured for Exelixis, Inc. Alameda, CA 94502

For more information, go to www.cometriq.com or call 1-855-292-3935.

This Patient Information has been approved by the U.S. Food and Drug Administration. Revised 10/2025

PACKAGE LABEL

Package Label - CARTON - 140 mg Daily Dose of COMETRIQ

PRINCIPAL DISPLAY PANEL

Cometriq®
(cabozantinib) capsules
140 mg Daily Dose
Blister Cards
Each 140 mg daily dose contains a combination of
one Swedish orange 80 mg and three grey 20 mg
capsules. Each capsule contains cabozantinib
(S)-malate equivalent to 80 mg or 20 mg of
cabozantinib.
EXELIXIS®
NDC 42388-011-14
Carton containing 4 blister cards:
The blister cards in this carton are for
patients prescribed a 140 mg daily dose.
Rx Only

PACKAGE LABEL

Package Label - CARTON - 100 mg Daily Dose of COMETRIQ

PRINCIPAL DISPLAY PANEL

Cometriq®
(cabozantinib) capsules
100 mg Daily Dose
Blister Cards
Each 100 mg daily dose contains a combination
of one Swedish orange 80 mg and one grey
20 mg capsule. Each capsule contains
cabozantinib (S)-malate equivalent to 80 mg
or 20 mg of cabozantinib.
EXELIXIS®
NDC 42388-012-14
Carton containing 4 blister cards:
The blister cards in this carton are for
patients prescribed a 100 mg daily dose.
Rx Only

PACKAGE LABEL

Package Label - CARTON - 60 mg Daily Dose of COMETRIQ

PRINCIPAL DISPLAY PANEL

Cometriq®
(cabozantinib) capsules
60 mg Daily Dose
Blister Cards
Each 60 mg daily dose contains three grey 20 mg
capsules. Each capsule contains cabozantinib
(S)-malate equivalent to 20 mg of cabozantinib.
EXELIXIS®
NDC 42388-013-14
Carton containing 4 blister cards:
The blister cards in this carton are for
patients prescribed a 60 mg daily dose.
Rx Only